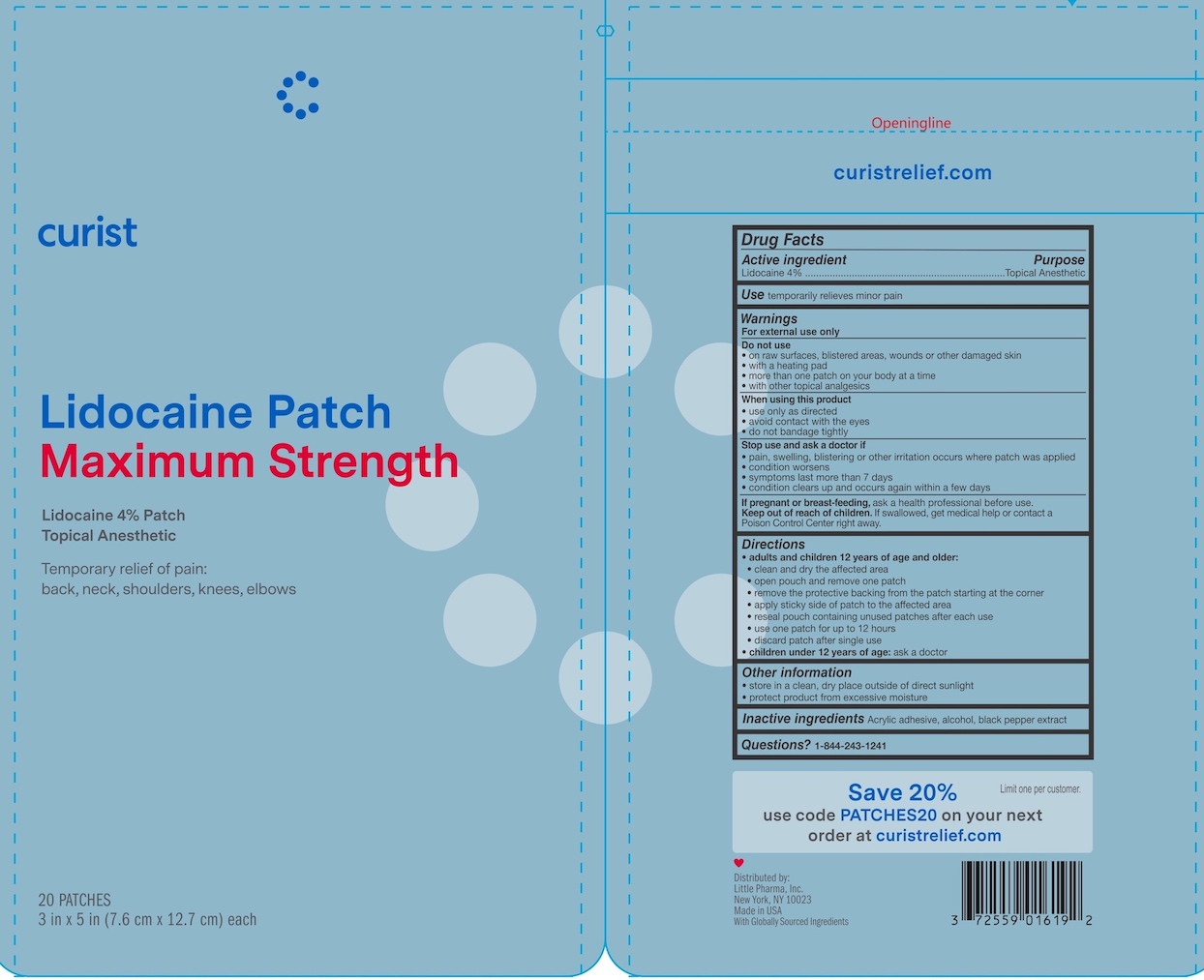 DRUG LABEL: Curist Lidocaine
NDC: 72559-016 | Form: PATCH
Manufacturer: Little Pharma, Inc.
Category: otc | Type: HUMAN OTC DRUG LABEL
Date: 20251208

ACTIVE INGREDIENTS: LIDOCAINE 4 g/100 g
INACTIVE INGREDIENTS: BLACK PEPPER; ACRYLIC ACID; ALCOHOL

Curist Lidocaine Patch

Drug Facts

Active ingredient

Lidocaine 4%

Purpose

Topical Anesthetic

Use

temporarily relieves minor pain

Warnings

For external use only

Do not use

- on raw surfaces, blistered areas, wounds or other damaged skin
- with a heating pad
- more than one patch on your body at a time
- with other topical anagesics

When using this product

- use only as directed
- avoid contact with the eyes
- do not bandage tightly

Stop use and ask a doctor if

- pain, swelling, blistering or other irritation occurs where patch was applied
- condition worsens
- symptoms last more than 7 days
- condition clears up and occurs again within a few days

PREGNANCY OR BREAST FEEDING

If pregnant or breastfeeding, ask a health professional before use.

Keep out of reach of children. If swallowed, get medical help or contact a Poison Control Center right away.

Directions

- adults and children 12 years of age and older:
- clean and dry the affected area
- open pouch and remove one patch
- remove the protective backing from the patch starting at the corner
- apply sticky side of patch to affected area
- reseal pouch containing unused patches after each use
- use one patch for up to 12 hours
- discard patch after single use
- children under 12 years of age: ask a doctor

Other information

- store in a clean, dry place outside of direct sunlight
- protect product from excessive moisture

Inactive ingredients

Acrylic adhesive, alcohol, black pepper extract

Questions?

1-844-243-1241

Distributed by:

Little Pharma, Inc.

New York, NY 10023

Made in USA With Globally Sourced Ingredients

PACKAGE LABEL

Curist

Lidocaine Patch Maximum Strength

Lidocaine 4% Patch

Topical Anesthetic

Temporary relief of pain: back, neck, shoulders, knees, elbows

20 PATCHES

3 in x 5 in (7.6 cm x 12.7 cm) each